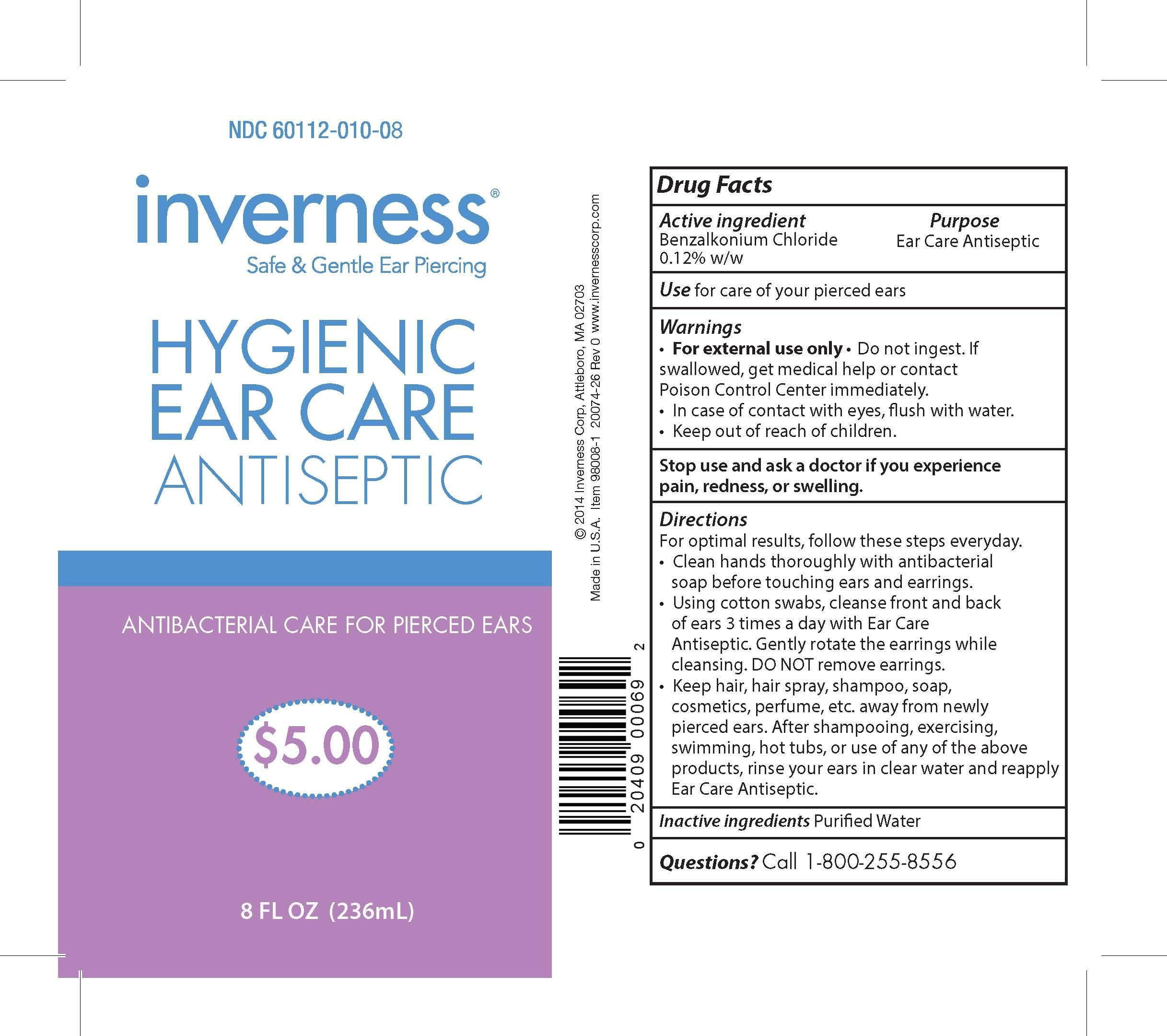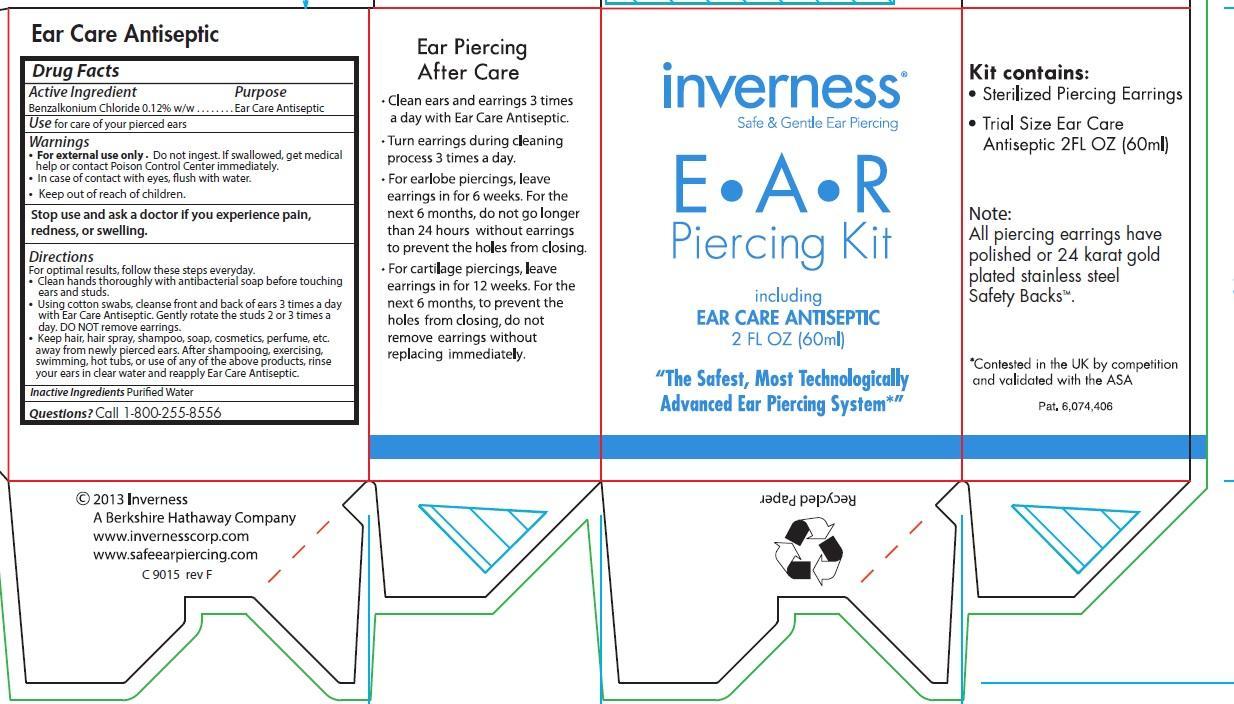 DRUG LABEL: Inverness EAR CARE ANTISEPTIC
NDC: 70094-010 | Form: SOLUTION
Manufacturer: The Richline Group
Category: otc | Type: HUMAN OTC DRUG LABEL
Date: 20250217

ACTIVE INGREDIENTS: BENZALKONIUM CHLORIDE 1.2 mg/1 mL
INACTIVE INGREDIENTS: WATER

Inverness EAR CARE ANTISEPTIC

Active Ingredient

Benzalkonium Chloride 0.12% w/w

Purpose

Ear Care Antiseptic

INDICATIONS AND USAGE

Use for care of your pierced ears

Warnings

- For external use only.
- Do not ingest.
- If swallowed, get medical help or contact Poison Control Center immediately.
- In case of contact with eyes, flush with water.

SEEK MEDICAL ATTENTION IF IRRITATION PERSISTS

- Keep out of reach of children.
- Pain, redness, or swelling is not a normal result of ear piercing.
- Call your doctor if any type of discomfort occurs.
- Remove earrings immediately.

Directions

For optimal results, follow these steps every day:

- Clean hands thoroughly with antibacterial soap before touching ears and earrings.
- Using cotton swab, cleanse front and back of ears 3 times a day with Ear Care Antiseptic. Gently rotate the earrings 2 or 3 times a day. DO NOT remove earrings.
- Keep hair, hair spray, shampoo, soap, cosmetics, perfume, etc. away from newly pierced ears. After shampooing, exercising, swimming, hot tubs, or use of any of the above products, rinse your ears in clear water and reapply Ear Care Antiseptic, (step 2), to your ears.

Other Information

EAR LOBE PIERCING

- Leave earrings in your ears for 6 weeks.
- After 6 weeks the earrings may be removed; however, some type of post earring must be worn at all time during the first 6 months.

EAR CARTILAGE PIERCING

- Leave earrings in your ears for 12 weeks.
- After 12 weeks the earrings may be removed; however, some type of post earring must be worn at all times during the first year.

Inactive Ingredient

Purified water.

Questions?

Call 1-800-255-8556